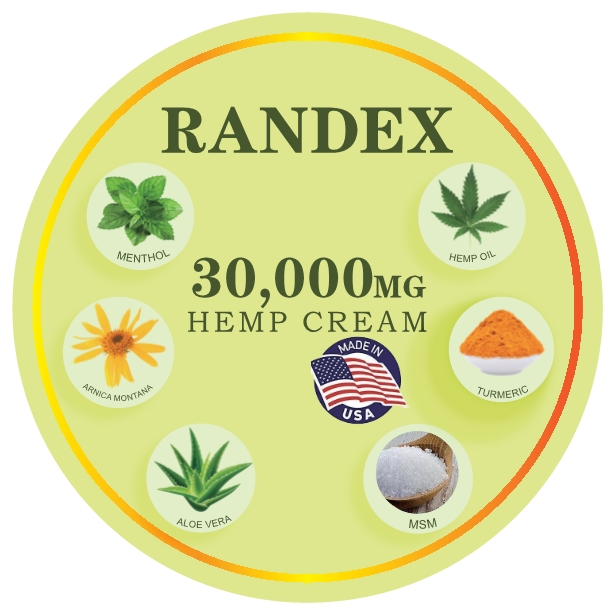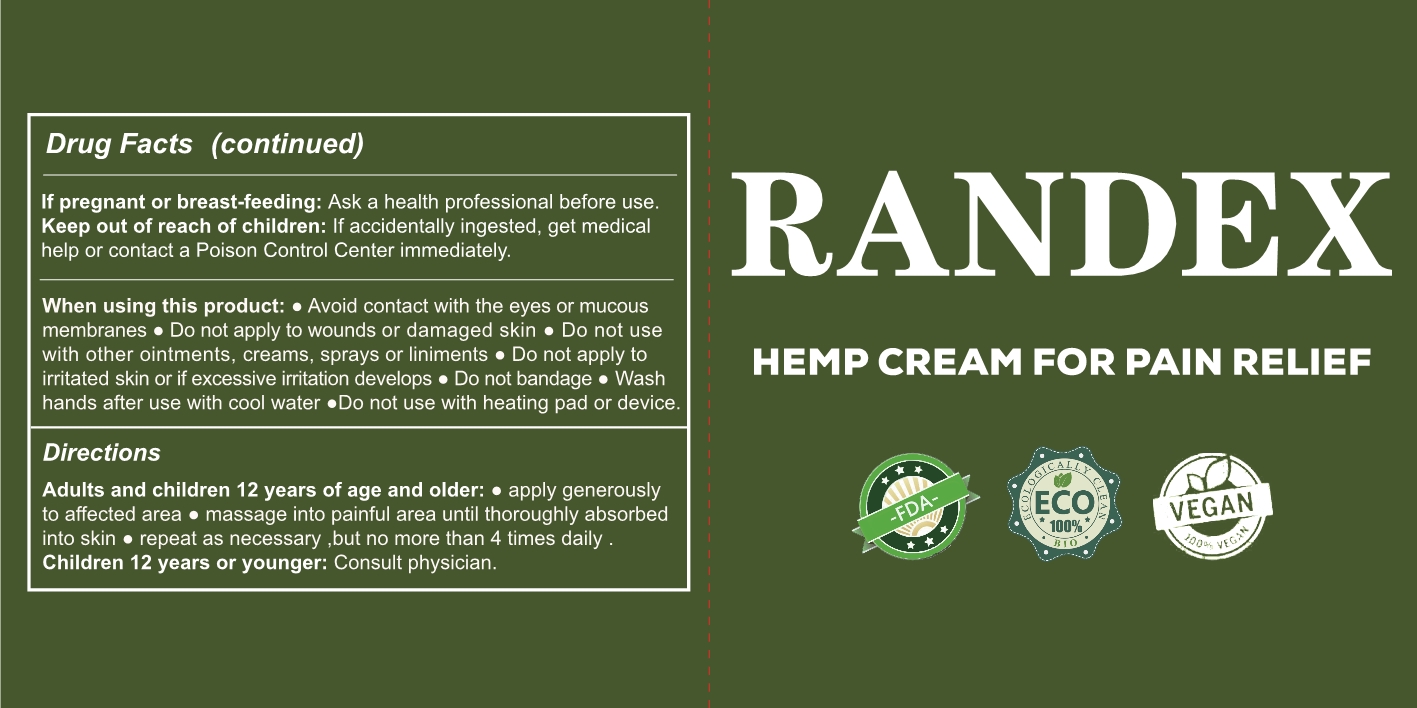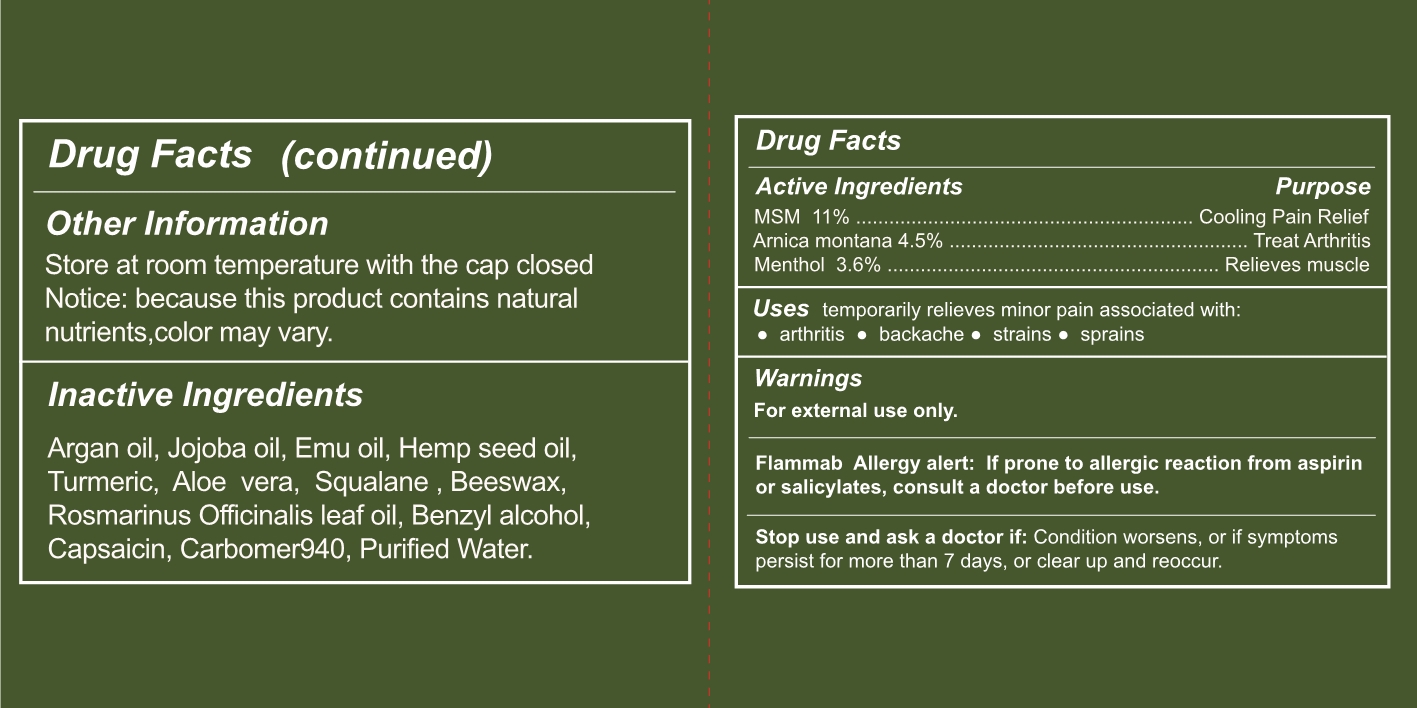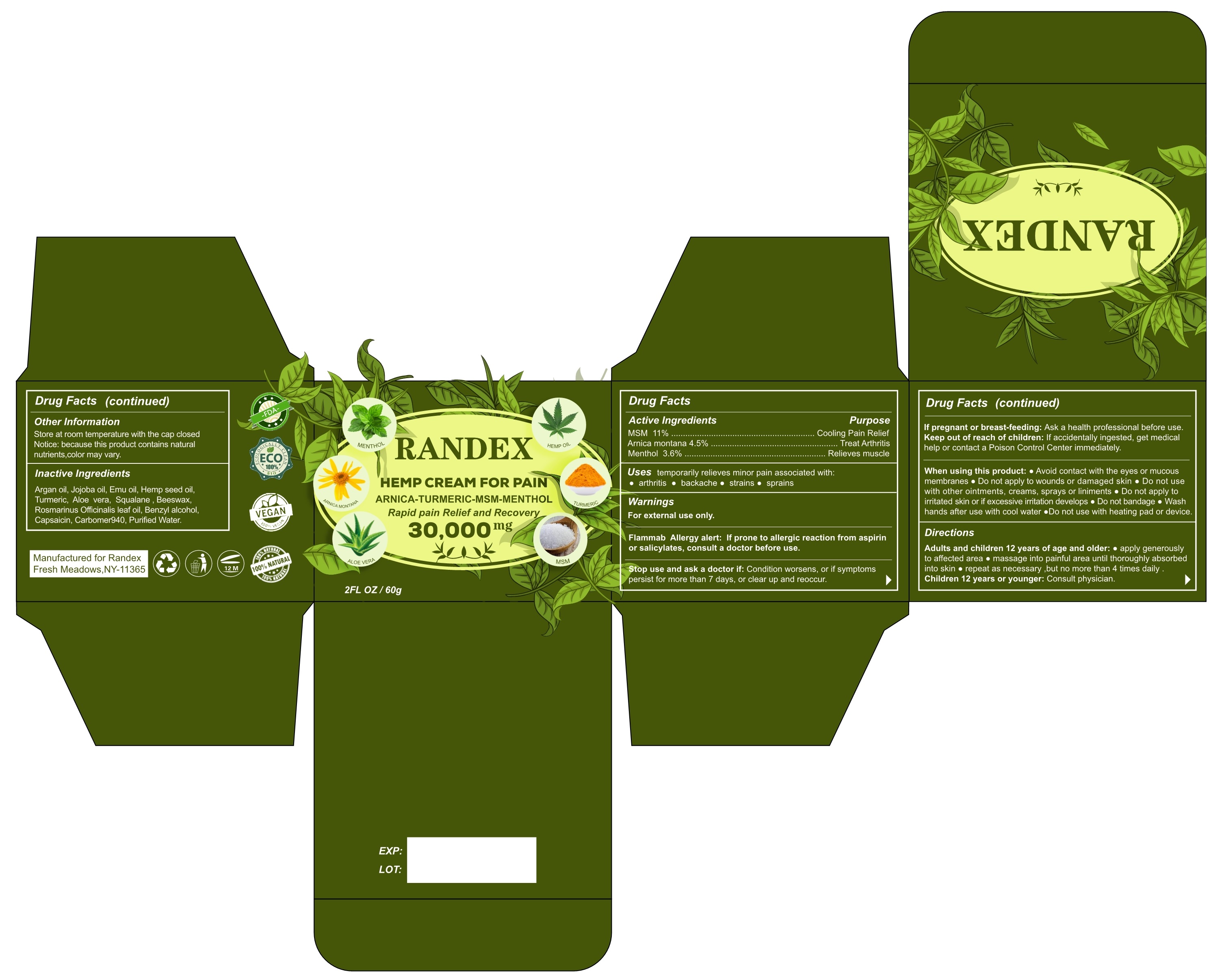 DRUG LABEL: RANDEX HEMP cream
NDC: 81852-001 | Form: CREAM
Manufacturer: Randex Trading Inc.
Category: otc | Type: HUMAN OTC DRUG LABEL
Date: 20210427

ACTIVE INGREDIENTS: ARNICA MONTANA FLOWER 4.5 mg/100 mg; DIMETHYL SULFONE 11 mg/100 mg; MENTHOL 3.6 mg/100 mg
INACTIVE INGREDIENTS: YELLOW WAX; CAPSAICIN; CARBOMER 940; WATER; SQUALANE; TURMERIC; ARGAN OIL; ALOE VERA LEAF; EMU OIL; CANNABIS SATIVA SEED OIL; ROSEMARY OIL; BENZYL ALCOHOL; JOJOBA OIL

81852-001
RANDEX HEMP cream

Active Ingredient(s)

MSM 11% ............................................................. Cooling Pain Relief
Arnica montana 4.5% ...................................................... Treat Arthritis
Menthol 3.6% ............................................................ Relieves muscle

Purpose

Active Ingredients Purpose
MSM 11% ............................................................. Cooling Pain Relief
Arnica montana 4.5% ...................................................... Treat Arthritis
Menthol 3.6% ............................................................ Relieves muscle

Use

Flammab Allergy alert: If prone to allergic reaction from aspirin or salicylates, consult a doctor before use.

Warnings

For external use only.

Flammab Allergy alert: If prone to allergic reaction from aspirin or salicylates, consult a doctor before use.

Stop use and ask a doctor if: Condition worsens, or if symptoms persist for more than 7 days, or clear up and reoccur.

If pregnant or breast-feeding: Ask a health professional before use.

Keep out of reach of children: If accidentally ingested, get medical help or contact a Poison Control Center immediately.

● Do not use with other ointments, creams, sprays or liniments
●Do not use with heating pad or device.

When using this product:
● Avoid contact with the eyes or mucous membranes
● Do not apply to wounds or damaged skin
● Do not use with other ointments, creams, sprays or liniments
● Do not apply to irritated skin or if excessive irritation develops
● Do not bandage
● Wash hands after use with cool water
● Do not use with heating pad or device.

Stop use and ask a doctor if: Condition worsens, or if symptoms persist for more than 7 days, or clear up and reoccur.

If pregnant or breast-feeding: Ask a health professional before use.

Keep out of reach of children: If accidentally ingested, get medical help or contact a Poison Control Center immediately.

Directions

Adults and children 12 years of age and older:
● apply generously to affected area
● massage into painful area until thoroughly absorbed into skin
● repeat as necessary ,but no more than 4 times daily .
Children 12 years or younger: Consult physician.

Other information

Store at room temperature with the cap closed
Notice: because this product contains natural nutrients,color may vary.

Inactive ingredients

Argan oil, Jojoba oil, Emu oil, Hempseed oil, Turmeric, Aloe vera, Squalane , Beeswax, Rosmarinus Officinalis leaf oil, Benzyl alcohol, Capsaicin, Carbomer940, Purified Water.

Package Label - Principal Display Panel

81852-001-01 30000mg in 1 box

81852-001 Directions 1

81852-001 label